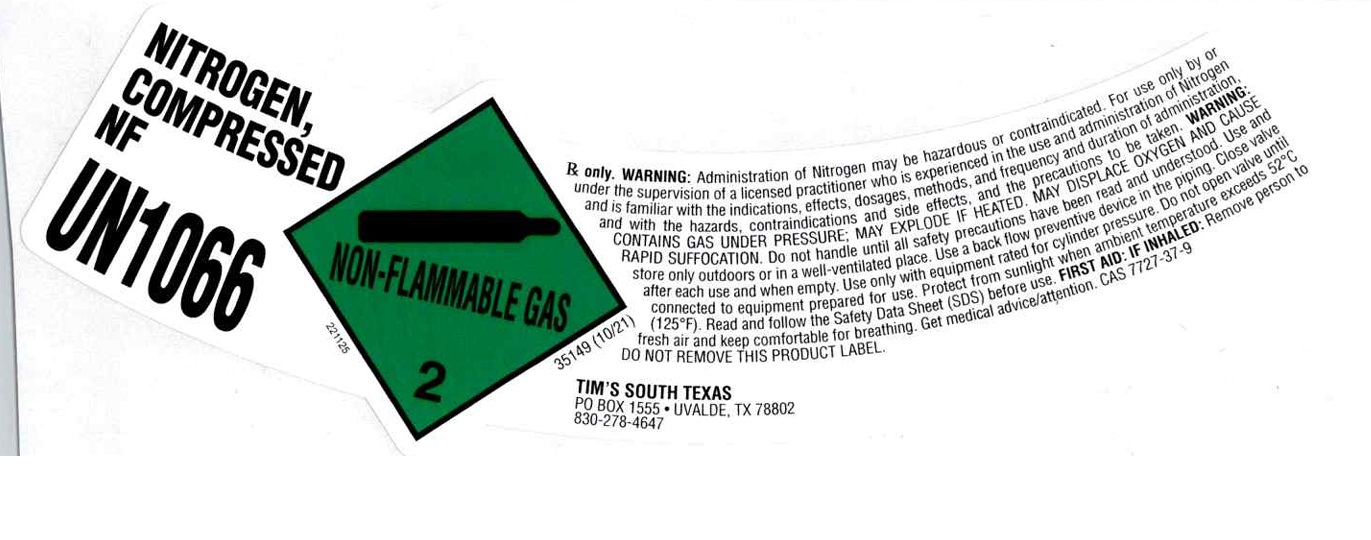 DRUG LABEL: Nitrogen
NDC: 71227-002 | Form: GAS
Manufacturer: TIMS SOUTH TEXAS LLC
Category: prescription | Type: HUMAN PRESCRIPTION DRUG LABEL
Date: 20251209

ACTIVE INGREDIENTS: NITROGEN 990 mL/1 L

Nitrogen

PACKAGE LABEL

NITROGEN, COMPRESSED NF

UN1066

Rx only. WARNING: Administration of Nitrogen may be hazardous or contraindicated. For use only by or under the supervision of a licensed practitioner who is experienced in the use and administration of Nitrogen and is familiar with the indications, effects, dosages, methods, and frequency and duration of administration, and with the hazards, contraindications and side effects, and the precautions to be taken. WARNING: CONTAINS GAS UNDER PRESSURE; MAY EXPLODE IF HEATED. MAY DISPLACE OXYGEN AND CAUSE RAPID SUFFOCATION. Do not handle until all safety precautions have been read and understood. Use and store only outdoors or in a well-ventilated place. Use a back flow preventive device in the piping. Close valve after each use and when empty. Use only with equipment rated for cylinder pressure. Do not open valve until connected to equipment prepared for use. Protect from sunlight when ambient temperature exceeds 52 C (125 F). Read and follow the Safety Data Sheet (SDS) before use. FIRST AID: IF INHALED: Remove person to fresh air and keep comfortable for breathing. Get medical advice/attention. CAS 7727-37-9

DO NOT REMOVE THIS PRODUCT LABEL.

TIM’S SOUTH TEXAS

PO BOX 1555 UVALDE, TX 78802

830-278-4647